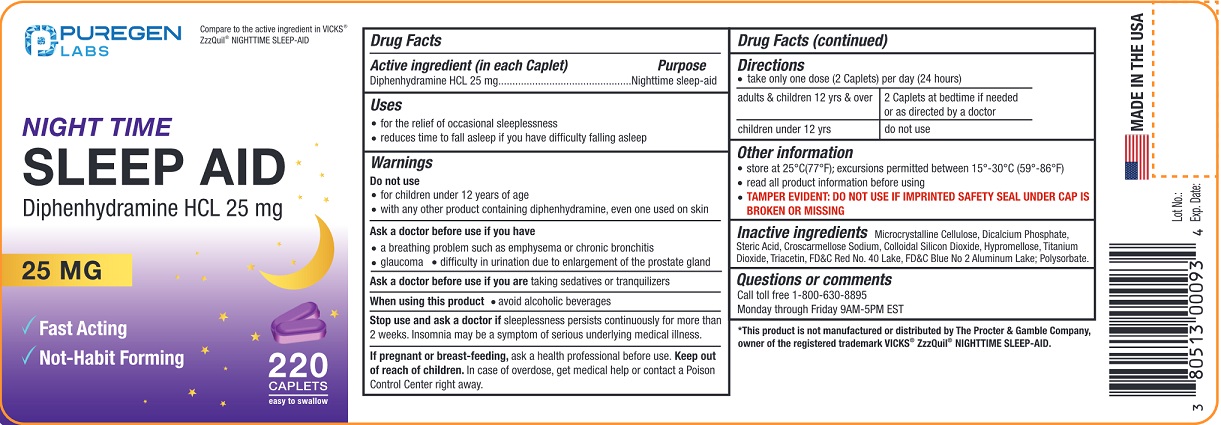 DRUG LABEL: NIGHT TIME SLEEP-AID
NDC: 80513-383 | Form: TABLET
Manufacturer: Advanced Rx LLC
Category: otc | Type: HUMAN OTC DRUG LABEL
Date: 20250702

ACTIVE INGREDIENTS: DIPHENHYDRAMINE HYDROCHLORIDE 25 mg/1 1
INACTIVE INGREDIENTS: MICROCRYSTALLINE CELLULOSE; ANHYDROUS DIBASIC CALCIUM PHOSPHATE; STEARIC ACID; CROSCARMELLOSE SODIUM; SILICON DIOXIDE; HYPROMELLOSE, UNSPECIFIED; TITANIUM DIOXIDE; TRIACETIN; FD&C RED NO. 40 ALUMINUM LAKE; FD&C BLUE NO. 2 ALUMINUM LAKE

NIGHT TIME SLEEP-AID

Drug Facts

Active ingredients (in each Caplet)

Diphenhydramine HCl 25 mg

Purpose

Nighttime sleep-aid

Uses

- for the relief of occasional sleeplessness
- reduces time to fall asleep if you have difficulty falling asleep

Warnings

Do not use

- for children under 12 years of age
- with any other product containing diphenhydramine, even one used on skin.

Ask a doctor before use if you have

- a breathing problem such as emphysema or chronic bronchitis
- glaucoma
- difficulty in urination due to enlargement of the prostate gland

Ask a doctor or pharmacist before use if you are taking sedatives or tranquilizers

When using this product

- avoid alcoholic beverages

Stop use and ask a doctor if sleeplessness persists continuously for more than 2 weeks. Insomnia may be a symptom of serious underlying medical illness.

PREGNANCY OR BREAST FEEDING

If pregnant or breast-feeding, ask a health professional before use.

Keep out of reach of children.

In case of overdose, get medical help or contact a Poison Control Center right away.

Directions

• take only one dose (2 Caplets) per day (24 hours)

adults & children 12 yrs & over | 2 Caplets at bedtime if needed or as directed by a doctor
children under 12 yrs | do not use

Other information

- store at 25°C (77°F); excursions permitted between 15°-30°C (59°-86°F)
- read all product information before using
- TAMPER EVIDENT: DO NOT USE IF IMPRINTED SAFETY SEAL UNDER CAP IS BROKEN OR MISSIN

Inactive ingredients

Microcrystalline Cellulose, Dicalcium Phosphate, Stearic Acid, Croscarmellose Sodium, Colloidal Silicon Dioxide, Hypromellose, Titanium Dioxide, Triacetin, FD&C Red No.40 Lake, FD&C Blue No.2 Aluminum Lake, Polysorbate.

Questions or comments

Call toll free 1-800-630-8895

Monday through Friday 9AM - 5PM EST

Distributed by:

Advanced Rx LLC

1942 NE 163rd St North Miami Beach,

FL 33162 U.S.A.

MADE IN THE USA

PRINCIPAL DISPLAY PANEL

NDC 80513-383-22

Compare to the active indredient in VICKS®ZzzQuil®NIGHTTIME SLEEP-AID*

NIGHT TIME SLEEP-AID

Diphenhydramine HCl 25 mg

220 CAPLETS

*This product is not manufactured or distributed by The The Procter & Gamble Company, owner of the registered trademark VICKS®ZzzQuil®NIGHTTIME SLEEP-AID